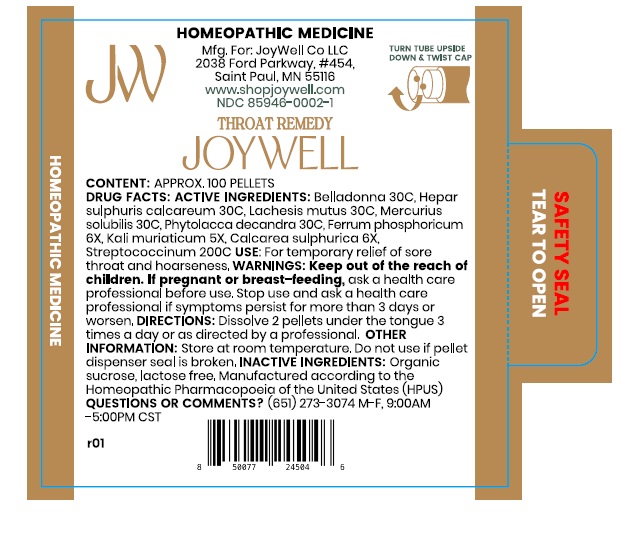 DRUG LABEL: Throat Remedy
NDC: 85946-0002 | Form: PELLET
Manufacturer: JoyWell Co LLC
Category: homeopathic | Type: HUMAN OTC DRUG LABEL
Date: 20251211

ACTIVE INGREDIENTS: ATROPA BELLADONNA 30 [hp_C]/1 1; CALCIUM SULFIDE 30 [hp_C]/1 1; LACHESIS MUTA VENOM 30 [hp_C]/1 1; MERCUROUS NITRATE 30 [hp_C]/1 1; PHYTOLACCA AMERICANA ROOT 30 [hp_C]/1 1; FERRIC PHOSPHATE 6 [hp_X]/1 1; POTASSIUM CHLORIDE 5 [hp_X]/1 1; CALCIUM SULFATE, UNSPECIFIED FORM 6 [hp_X]/1 1; STREPTOCOCCUS PYOGENES 200 [hp_C]/1 1
INACTIVE INGREDIENTS: SUCROSE

Active ingredients

Belladonna 30C, Hear sulphuris calcareum 30C, Lachesis mutus 30C, Mercurius solubilis 30C, Phytolacca decandra 30C, Ferrum phosphoricum
6X, Kali muriaticum 5X, Calcarea sulphurica 6X, Streptococcinum 200C

Uses

For temporary relief of sore throat and hoarseness.

Warnings

Keep out of the reach of children. If pregnant or breast-feeding, ask a health care professional before use.Stop use and ask a health care professional if symptoms persist for more than 3 days or worsen.

Directions

Dissolve 2 pellets under the tongue 3 times a day or as directed by a professional.

Other informmation

Store at room temperature. Do not use if pellet dispenser seal is broken.

Inactive ingredients

Organic sucrose

Lactose-free Manufactured according to the Homeopathic Pharmacopoeia of the United States (HPUS).

QUESTIONS OR COMMENTS?

(651) 273-3074 M-F, 9:00AM -5:00PM CST